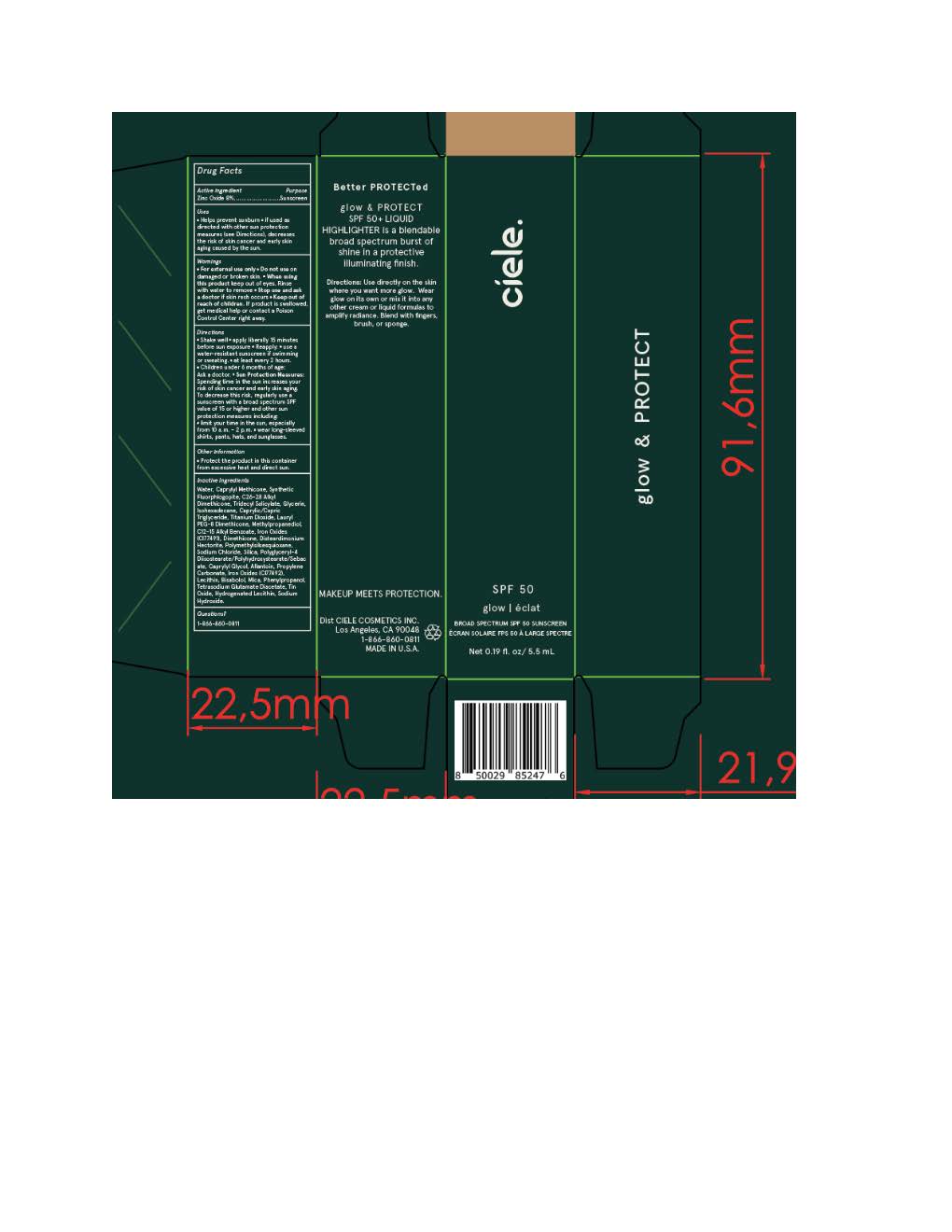 DRUG LABEL: Ciele Glow and Protect
NDC: 83103-2344 | Form: LOTION
Manufacturer: Ciele Cosmetics
Category: otc | Type: HUMAN OTC DRUG LABEL
Date: 20251015

ACTIVE INGREDIENTS: ZINC OXIDE 88 mg/1 mL
INACTIVE INGREDIENTS: ISOHEXADECANE; LECITHIN, SOYBEAN; METHYLPROPANEDIOL; CAPRYLYL GLYCOL; POLYGLYCERYL-4 DIISOSTEARATE/POLYHYDROXYSTEARATE/SEBACATE; .ALPHA.-BISABOLOL, (+)-; WATER; TETRASODIUM GLUTAMATE DIACETATE; SODIUM CHLORIDE; ALLANTOIN; POLYMETHYLSILSESQUIOXANE (4.5 MICRONS); LAURYL PEG-8 DIMETHICONE (300 CPS); FERRIC OXIDE RED; ALKYL (C12-15) BENZOATE; CAPRYLYL METHICONE; DIMETHICONE; FERROSOFERRIC OXIDE; FERRIC OXIDE YELLOW; TRIDECYL SALICYLATE; TIN OXIDE; SILICON DIOXIDE; HYDROGENATED SOYBEAN LECITHIN; SODIUM HYDROXIDE; PHENYLPROPANOL; GLYCERIN; TITANIUM DIOXIDE; MICA; CAPRYLIC/CAPRIC TRIGLYCERIDE; DISTEARDIMONIUM HECTORITE

Ciele Glow and Protect